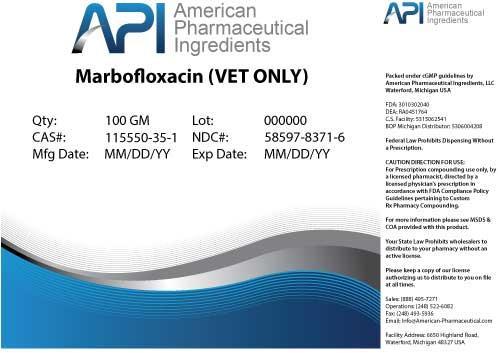 DRUG LABEL: Marbofloxacin
NDC: 58597-8371 | Form: POWDER
Manufacturer: AMERICAN PHARMACEUTICAL INGREDIENTS LLC
Category: other | Type: BULK INGREDIENT
Date: 20140428

ACTIVE INGREDIENTS: Marbofloxacin 1 g/1 g

Marbofloxacin